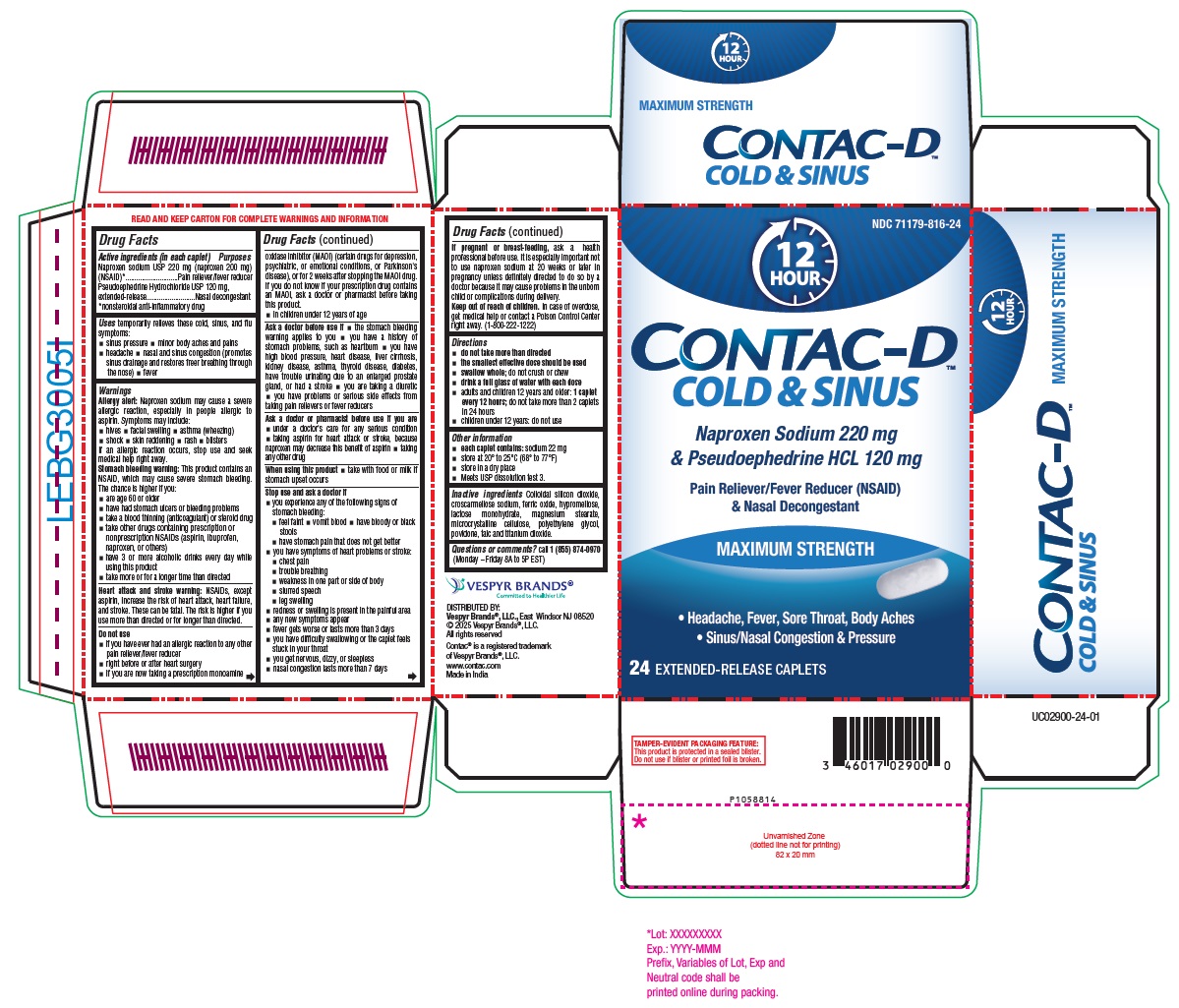 DRUG LABEL: NAPROXEN SODIUM AND PSEUDOEPHEDRINE HYDROCHLORIDE COLD AND SINUS
NDC: 71179-816 | Form: TABLET, EXTENDED RELEASE
Manufacturer: VESPYR BRANDS, INC.
Category: otc | Type: Human OTC Drug Label
Date: 20250607

ACTIVE INGREDIENTS: NAPROXEN SODIUM 220 mg/1 1; PSEUDOEPHEDRINE HYDROCHLORIDE 120 mg/1 1
INACTIVE INGREDIENTS: SILICON DIOXIDE; CROSCARMELLOSE SODIUM; FERRIC OXIDE YELLOW; HYPROMELLOSE 2208 (15000 MPA.S); HYPROMELLOSE, UNSPECIFIED; HYPROMELLOSE 2910 (6 MPA.S); LACTOSE MONOHYDRATE; MAGNESIUM STEARATE; MICROCRYSTALLINE CELLULOSE 101; MICROCRYSTALLINE CELLULOSE 102; POLYETHYLENE GLYCOL 4000; POVIDONE K30; TALC; TITANIUM DIOXIDE

Naproxen Sodium and Pseudoephedrine Hydrochloride Extended-Release Tablets, USP 220 mg/120 mg Sinus and Cold
Drug Facts

Active ingredients (in each caplet)

Naproxen sodium USP 220 mg (naproxen 200 mg) (NSAID)*
Pseudoephedrine Hydrochloride USP 120 mg, extended-release
*nonsteroidal anti-inflammatory drug

Purposes

Pain reliever/fever reducer
Nasal decongestant

Uses

temporarily relieves these cold, sinus, and flu symptoms:

- sinus pressure
- minor body aches and pains
- headache
- nasal and sinus congestion (promotes sinus drainage and restores freer breathing through the nose)
- fever

Warnings

Allergy alert: Naproxen sodium may cause a severe allergic reaction, especially in people allergic to aspirin. Symptoms may include:

- hives
- facial swelling
- asthma (wheezing)
- shock
- skin reddening
- rash
- blisters

If an allergic reaction occurs, stop use and seek medical help right away.

Stomach bleeding warning: This product contains an NSAID, which may cause severe stomach bleeding. The chance is higher if you:

- are age 60 or older
- have had stomach ulcers or bleeding problems
- take a blood thinning (anticoagulant) or steroid drug
- take other drugs containing prescription or nonprescription NSAIDs (aspirin, ibuprofen, naproxen, or others)
- have 3 or more alcoholic drinks every day while using this product
- take more or for a longer time than directed

Heart attack and stroke warning: NSAIDs, except aspirin, increase the risk of heart attack, heart failure, and stroke. These can be fatal. The risk is higher if you use more than directed or for longer than directed.

Do not use

- if you have ever had an allergic reaction to any other pain reliever/fever reducer
- right before or after heart surgery
- if you are now taking a prescription monoamine oxidase inhibitor (MAOI) (certain drugs for depression, psychiatric, or emotional conditions, or Parkinson's disease), or for 2 weeks after stopping the MAOI drug. If you do not know if your prescription drug contains an MAOI, ask a doctor or pharmacist before taking this product.
- in children under 12 years of age

Ask a doctor before use if

- the stomach bleeding warning applies to you
- you have a history of stomach problems, such as heartburn
- you have high blood pressure, heart disease, liver cirrhosis, kidney disease, asthma, thyroid disease, diabetes, have trouble urinating due to an enlarged prostate gland, or had a stroke
- you are taking a diuretic
- you have problems or serious side effects from taking pain relievers or fever reducers

Ask a doctor or pharmacist before use if you are

- under a doctor's care for any serious condition
- taking aspirin for heart attack or stroke, because naproxen may decrease this benefit of aspirin
- taking any other drug

When using this product

- take with food or milk if stomach upset occurs

Stop use and ask a doctor if

- you experience any of the following signs of stomach bleeding:
  - feel faint
  - vomit blood
  - have bloody or black stools
  - have stomach pain that does not get better
- you have symptoms of heart problems or stroke:
  - chest pain
  - trouble breathing
  - weakness in one part or side of body
  - slurred speech
  - leg swelling
- redness or swelling is present in the painful area
- any new symptoms appear
- fever gets worse or lasts more than 3 days
- you have difficulty swallowing or the caplet feels stuck in your throat
- you get nervous, dizzy, or sleepless
- nasal congestion lasts more than 7 days

If pregnant or breast-feeding,

ask a health professional before use. It is especially important not to use naproxen sodium at 20 weeks or later in pregnancy unless definitely directed to do so by a doctor because it may cause problems in the unborn child or complications during delivery.

Keep out of reach of children.

In case of overdose, get medical help or contact a Poison Control Center right away. (1-800-222-1222)

Directions

- do not take more than directed
- the smallest effective dose should be used
- swallow whole; do not crush or chew
- drink a full glass of water with each dose
- adults and children 12 years and older: 1 caplet every 12 hours; do not take more than 2 caplets in 24 hours
- children under 12 years: do not use

Other information

- each caplet contains: sodium 22 mg
- store at 20° to 25°C (68° to 77°F)
- store in a dry place
- Meets USP dissolution test 3.

Inactive ingredients

Colloidal silicon dioxide, croscarmellose sodium, ferric oxide, hypromellose, lactose monohydrate, magnesium stearate, microcrystalline cellulose, polyethylene glycol, povidone, talc and titanium dioxide.

Questions or comments?

call 1 (855) 874-0970 (Monday – Friday 8A to 5P EST)
DISTRIBUTED BY:
Vespyr Brands®, LLC.,
East Windsor NJ 08520
© 2025 Vespyr Brands®, LLC.
All rights reserved
Contac® is a registered trademark
of Vespyr Brands®, LLC.
www.contac.com
Made in India

PACKAGE LABEL-PRINCIPAL DISPLAY PANEL - 220 mg / 120 mg 24 Caplets (Capsule-Shaped Tablets) Blister Carton Label

NDC 71179-816-24
12
HOUR
CONTAC-D™
COLD & SINUS
Naproxen Sodium 220 mg
& Pseudoephedrine HCL 120 mg
Pain Reliever/Fever Reducer (NSAID)
& Nasal Decongestant
MAXIMUM STRENGTH

- Headache, Fever, Sore Throat, Body Aches
- Sinus/Nasal Congestion & Pressure

24 EXTENDED-RELEASE CAPLETS